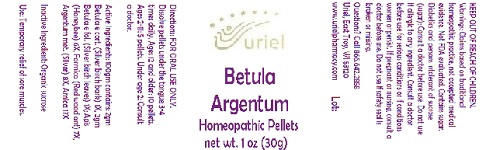 DRUG LABEL: Betula Argentum
NDC: 48951-2064 | Form: PELLET
Manufacturer: Uriel Pharmacy Inc.
Category: homeopathic | Type: HUMAN OTC DRUG LABEL
Date: 20180531

ACTIVE INGREDIENTS: BETULA PUBESCENS BARK 1 [hp_X]/1 1; BETULA PUBESCENS LEAF 1 [hp_X]/1 1; APIS MELLIFERA 6 [hp_X]/1 1; FORMICA RUFA 7 [hp_X]/1 1; SILVER 8 [hp_X]/1 1; ARNICA MONTANA 17 [hp_X]/1 1
INACTIVE INGREDIENTS: SUCROSE

Betula Argentum

INDICATIONS AND USAGE

Directions: FOR ORAL USE ONLY.

DOSAGE AND ADMINISTRATION

Dissolve pellets under the tongue 3-4 times daily. Ages 12 and older: 10 pellets. Ages 2-11: 5 pellets. Under age 2: Consult a doctor.

ACTIVE INGREDIENT

Active Ingredients: 100gm contains: 2gm Betula e cort. (Silver birch bark) 1X, 2gm Betula e fol. (Silver birch leaves) 1X; Apis (Honeybee) 6X, Formica (Red wood ant) 7X, Argentum met. (Silver) 8X, Arnica 17X

Inactive Ingredient: Organic sucrose

PURPOSE

Use: Temporary relief of sore muscles.

KEEP OUT OF REACH OF CHILDREN.

WARNINGS

Warnings: Claims based on traditional homeopathic practice, not accepted medical evidence. Not FDA evaluated. Contains sugar. Diabetics and persons intolerant of sucrose (sugar): Consult a doctor before use. Do not use if allergic to any ingredient. Consult a doctor before use for serious conditions or if conditions worsen or persist. If pregnant or nursing, consult a doctor before use. Do not use if safety seal is broken or missing.

QUESTIONS

Questions? Call 866.642.2858 Uriel, East Troy, WI 53120 www.urielpharmacy.com